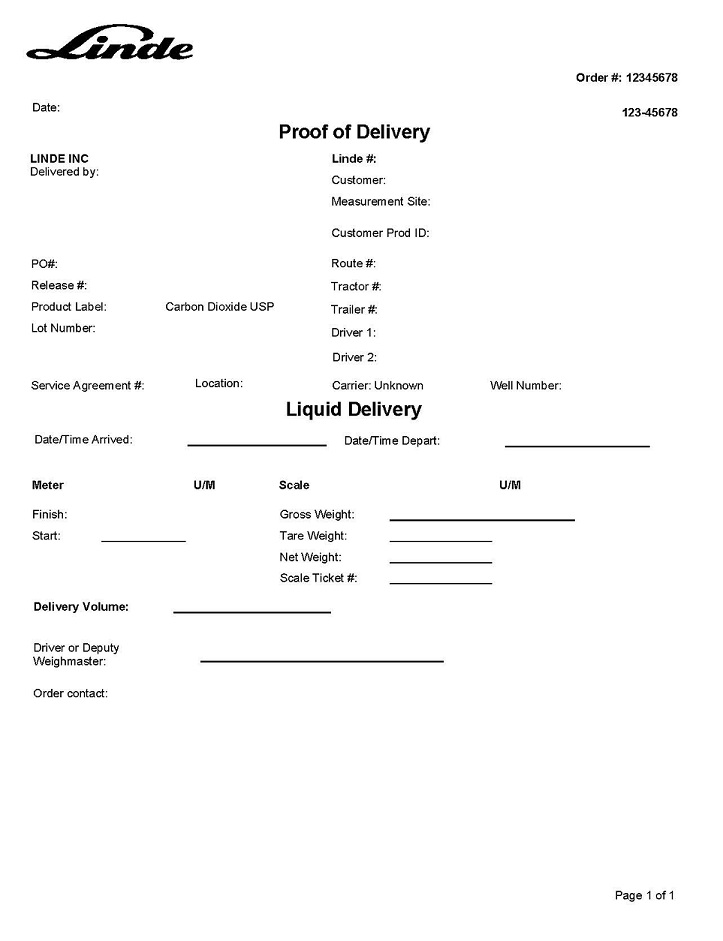 DRUG LABEL: Carbon Dioxide
NDC: 59578-125 | Form: GAS
Manufacturer: Linde Inc.
Category: prescription | Type: HUMAN PRESCRIPTION DRUG LABEL
Date: 20251230

ACTIVE INGREDIENTS: CARBON DIOXIDE 990 mL/1 L

Carbon Dioxide USP